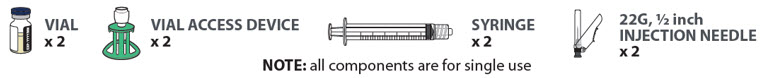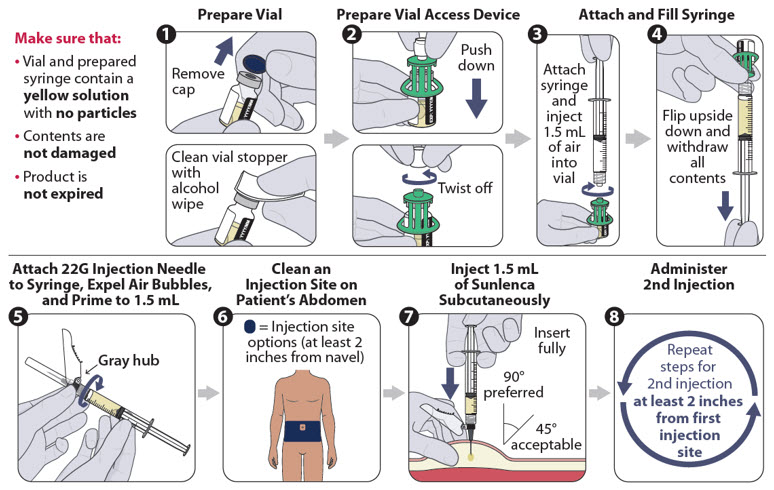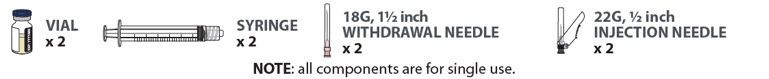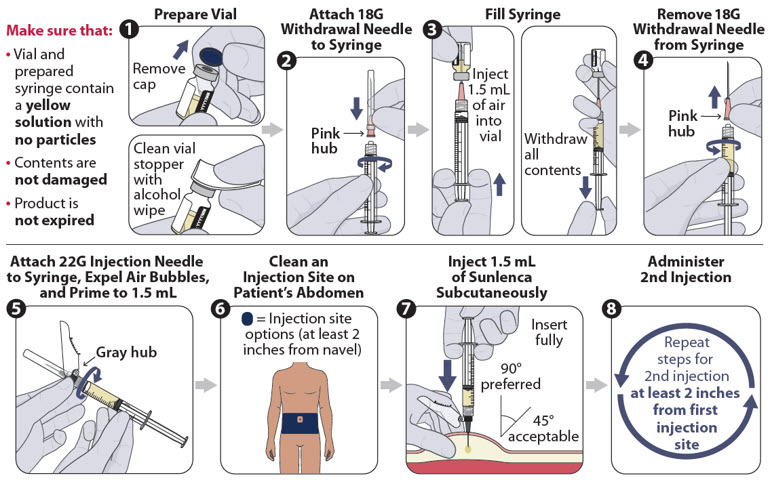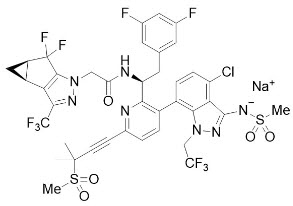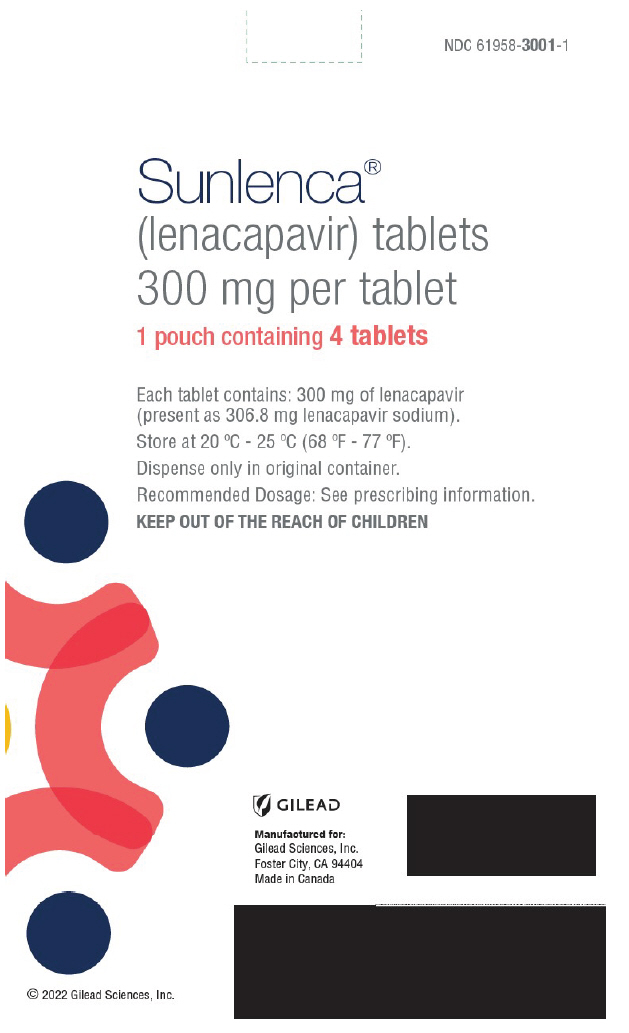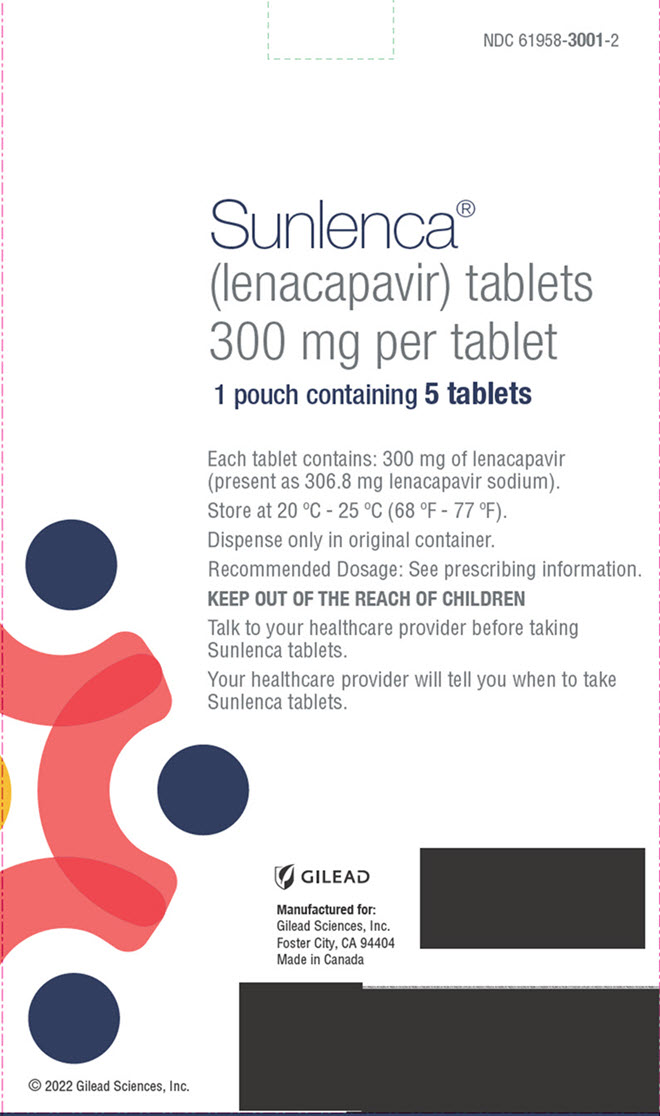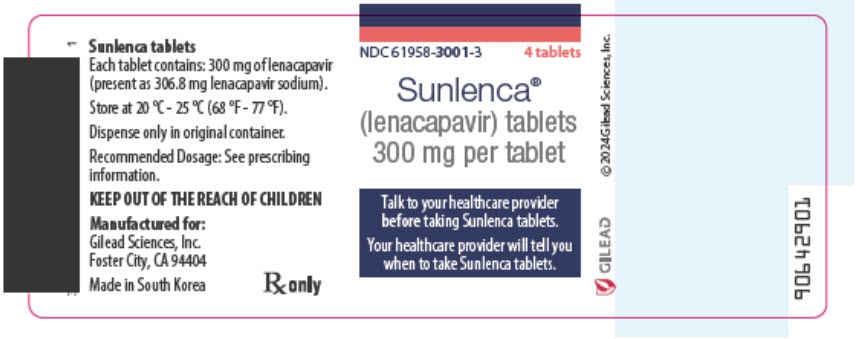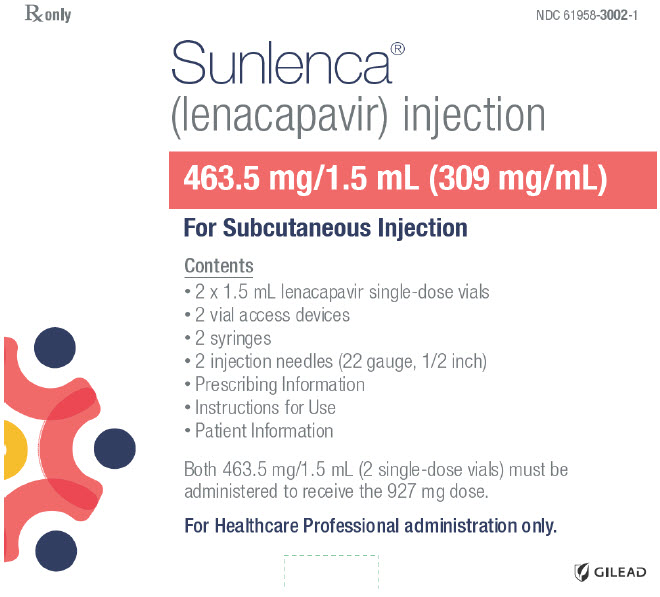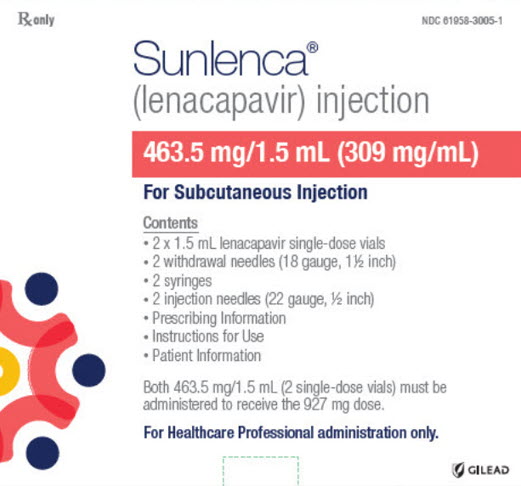 DRUG LABEL: Sunlenca
NDC: 61958-3001 | Form: TABLET, FILM COATED
Manufacturer: Gilead Sciences, Inc.
Category: prescription | Type: HUMAN PRESCRIPTION DRUG LABEL
Date: 20260212

ACTIVE INGREDIENTS: LENACAPAVIR SODIUM 300 mg/1 1
INACTIVE INGREDIENTS: COPOVIDONE K25-31; POLOXAMER 407; METHYL ALCOHOL; MANNITOL; MICROCRYSTALLINE CELLULOSE; CROSCARMELLOSE SODIUM; MAGNESIUM STEARATE

HIGHLIGHTS OF PRESCRIBING INFORMATION

These highlights do not include all the information needed to use SUNLENCA safely and effectively. See full prescribing information for SUNLENCA.
SUNLENCA® (lenacapavir) tablets, for oral use
SUNLENCA® (lenacapavir) injection, for subcutaneous use
Initial U.S. Approval: 2022

RECENT MAJOR CHANGES

Dosage and Administration (2.1, 2.3, 2.4) | 11/2024
Warnings and Precautions (5.3) | 11/2024

1 INDICATIONS AND USAGE

SUNLENCA, a human immunodeficiency virus type 1 (HIV-1) capsid inhibitor, in combination with other antiretroviral(s), is indicated for the treatment of HIV-1 infection in heavily treatment-experienced adults with multidrug resistant HIV-1 whose current antiretroviral regimen is failing due to resistance, intolerance, or safety considerations. (1)

2 DOSAGE AND ADMINISTRATION

- Recommended dosage – Initiation with one of two options followed by once every 6 months maintenance injection dosing. Tablets may be taken without regard to food. (2.2)

Initiation Option 1
Day 1 | 927 mg by subcutaneous injection (2 × 1.5 mL injections) 600 mg orally (2 × 300 mg tablets)
Day 2 | 600 mg orally (2 × 300 mg tablets)
Initiation Option 2
Day 1 | 600 mg orally (2 × 300 mg tablets)
Day 2 | 600 mg orally (2 × 300 mg tablets)
Day 8 | 300 mg orally (1 × 300 mg tablet)
Day 15 | 927 mg by subcutaneous injection (2 × 1.5 mL injections)
Maintenance
927 mg by subcutaneous injection (2 × 1.5 mL injections) every 6 months (26 weeks) from the date of the last injection +/-2 weeks.

- Planned missed injections: If scheduled injection is to be missed by more than 2 weeks, SUNLENCA tablets may be used for oral bridging for up to 6 months until injections resume. Recommended dosage is 300 mg orally once every 7 days. (2.3)
- Unplanned missed injections: If more than 28 weeks since last injection and tablets have not been taken for oral bridging, restart initiation from Day 1 (using Option 1 or Option 2) if clinically appropriate. (2.3)
- SUNLENCA injection is for subcutaneous administration only. Two 1.5 mL injections are required for complete dose. (2.4)

3 DOSAGE FORMS AND STRENGTHS

Tablets: 300 mg

Injection: 463.5 mg/1.5 mL (309 mg/mL) in single-dose vials. (3)

4 CONTRAINDICATIONS

Concomitant administration of SUNLENCA is contraindicated with strong CYP3A inducers. (4)

5 WARNINGS AND PRECAUTIONS

- Immune reconstitution syndrome: May necessitate further evaluation and treatment. (5.1)
- Residual concentrations of lenacapavir may remain in systemic circulation for up to 12 months or longer. Counsel patients regarding the dosing schedule; non-adherence could lead to loss of virologic response and development of resistance. (5.2)
- May increase exposure and risk of adverse reactions to drugs primarily metabolized by CYP3A initiated within 9 months after the last subcutaneous dose of SUNLENCA. (5.2)
- If discontinued, initiate an alternative, fully suppressive antiretroviral regimen where possible no later than 28 weeks after the final injection of SUNLENCA. If virologic failure occurs, switch to an alternative regimen if possible. (5.2)
- Injection site reactions may occur, and nodules and indurations may be persistent. Improper administration (intradermal injection) has been associated with serious injection site reactions. (5.3)

6 ADVERSE REACTIONS

Most common adverse reactions (incidence greater than or equal to 3%, all grades) are nausea and injection site reactions. (6.1)

To report SUSPECTED ADVERSE REACTIONS, contact Gilead Sciences, Inc. at 1-800-GILEAD-5 or FDA at 1-800-FDA-1088 or www.fda.gov/medwatch.

7 DRUG INTERACTIONS

- Consult the Full Prescribing Information prior to and during treatment for important drug interactions. (4, 7, 12.3)

FULL PRESCRIBING INFORMATION

1 INDICATIONS AND USAGE

SUNLENCA, in combination with other antiretroviral(s), is indicated for the treatment of human immunodeficiency virus type 1 (HIV-1) infection in heavily treatment-experienced adults with multidrug resistant HIV-1 whose current antiretroviral regimen is failing due to resistance, intolerance, or safety considerations.

2 DOSAGE AND ADMINISTRATION

2.1 Adherence to Treatment Regimen

Prior to starting SUNLENCA, healthcare providers should carefully select patients who agree to the required every 6 month injection dosing schedule and counsel patients about the importance of adherence to scheduled SUNLENCA dosing visits and concomitant oral antiretroviral therapy to help maintain viral suppression and reduce the risk of viral rebound and potential development of resistance with missed doses [see Warnings and Precautions (5.2), Microbiology (12.4)].

2.2 Recommended Dosage

SUNLENCA can be initiated using one of the two recommended dosage regimens in Table 1 and Table 2 below. Maintenance dosing is administered by subcutaneous injection every 6 months regardless of the initiation regimen. Healthcare providers should determine the appropriate initiation regimen for the patient. SUNLENCA oral tablets may be taken with or without food [see Clinical Pharmacology (12.3)].

Table 1 Recommended Treatment Regimen for SUNLENCA Initiation and Maintenance, Option 1
Treatment Time
 | Dosage of SUNLENCA: Initiation
Day 1 | 927 mg by subcutaneous injection (2 × 1.5 mL injections) 600 mg orally (2 × 300 mg tablets)
Day 2 | 600 mg orally (2 × 300 mg tablets)
 | Dosage of SUNLENCA: Maintenance
Every 6 months (26 weeks) [From the date of the last injection.] +/-2 weeks | 927 mg by subcutaneous injection (2 × 1.5 mL injections)

Table 2 Recommended Treatment Regimen for SUNLENCA Initiation and Maintenance, Option 2
Treatment Time
 | Dosage of SUNLENCA: Initiation
Day 1 | 600 mg orally (2 × 300 mg tablets)
Day 2 | 600 mg orally (2 × 300 mg tablets)
Day 8 | 300 mg orally (1 × 300 mg tablet)
Day 15 | 927 mg by subcutaneous injection (2 × 1.5 mL injections)
 | Dosage of SUNLENCA: Maintenance
Every 6 months (26 weeks) [From the date of the last injection.] +/-2 weeks | 927 mg by subcutaneous injection (2 × 1.5 mL injections)

2.3 Recommended Dosing Schedule for Missed Dose

Planned Missed Injections

During the maintenance period, if a patient plans to miss a scheduled 6-month injection visit by more than 2 weeks, SUNLENCA tablets may be taken for up to 6 months until injections resume. Refer to Table 3 below for the recommended dosage after planned missed injections.

Table 3 Recommended Dosage after Planned Missed Injections: Weekly Oral Maintenance
Time since Last Injection | Recommendation
26 to 28 weeks | Maintenance oral dosage of 300 mg taken once every 7 days for up to 6 months. Resume the maintenance injection dosage within 7 days after the last oral dose.

Unplanned Missed Injections

Patients who miss a scheduled injection visit should be clinically reassessed, including consideration of lenacapavir resistance testing, to ensure resumption of therapy remains appropriate. During the maintenance period, if more than 28 weeks have elapsed since the last injection and SUNLENCA tablets have not been taken, see Table 4 below for the recommended dosage after unplanned missed injections. Adherence to the injection dosing schedule is strongly recommended [see Dosage and Administration (2.1) and Microbiology (12.4)].

Table 4 Recommended Dosage after Unplanned Missed Injections
Time since Last Injection | Recommendation
More than 28 weeks | Reinitiate with Option 1 (Table 1) or Option 2 (Table 2) and then continue with maintenance injection dosing.

2.4 Preparation and Administration of Subcutaneous Injection

SUNLENCA injection is only for subcutaneous administration into the abdomen by a healthcare provider. Do NOT administer intradermally due to risk of serious injection site reactions [see Warnings and Precautions (5.3)].

Use aseptic technique. Visually inspect the solution in the vials and prepared syringe for particulate matter and discoloration prior to administration. SUNLENCA injection is a yellow solution. Do not use SUNLENCA injection if the solution is discolored or if it contains particulate matter. Once the solution is withdrawn from the vials, the subcutaneous injections should be administered as soon as possible [see How Supplied/Storage and Handling (16)].

There are two available injection kits, which differ only in how SUNLENCA injection is prepared (the components and associated method for withdrawal of the solution from the vials) [see How Supplied/Storage and Handling (16)]. Refer to the figures below for the relevant injection kit.

The injection kit components are for single use only. Two 1.5 mL injections are required for a complete dose.

Vial access device injection kit

Figure 1 identifies the components for use in the administration steps for the vial access device injection kit, and the administration steps are provided in Figure 2. Use of a vial access device is required in this kit.

Figure 1 SUNLENCA Vial Access Device Injection Kit Components

Figure 2 SUNLENCA Injection Steps for Vial Access Device Injection Kit

Withdrawal needle injection kit

Figure 3 identifies the components for use in the administration steps for the withdrawal needle injection kit, and the administration steps are provided in Figure 4. The 18-gauge needle is for withdrawal only in this kit.

Figure 3 SUNLENCA Withdrawal Needle Injection Kit Components

Figure 4 SUNLENCA Injection Steps for Withdrawal Needle Injection Kit

3 DOSAGE FORMS AND STRENGTHS

SUNLENCA tablets: Each tablet contains 300 mg of lenacapavir (present as 306.8 mg of lenacapavir sodium). The tablets are beige, capsule-shaped, film-coated, and debossed with 'GSI' on one side of the tablet and '62L' on the other side of the tablet.

SUNLENCA injection: Each single-dose vial contains 463.5 mg/1.5 mL (309 mg/mL) of lenacapavir (present as 473.1 mg/1.5 mL of lenacapavir sodium). The lenacapavir injectable solution is sterile, preservative-free, clear, and yellow with no visible particles.

4 CONTRAINDICATIONS

Concomitant administration of SUNLENCA with strong CYP3A inducers is contraindicated due to decreased lenacapavir plasma concentrations, which may result in the loss of therapeutic effect and development of resistance to SUNLENCA [see Drug Interactions (7.1)].

5 WARNINGS AND PRECAUTIONS

5.1 Immune Reconstitution Syndrome

Immune reconstitution syndrome has been reported in patients treated with combination antiretroviral therapy. During the initial phase of combination antiretroviral treatment, patients whose immune system responds may develop an inflammatory response to indolent or residual opportunistic infections [such as Mycobacterium avium infection, cytomegalovirus, Pneumocystis jirovecii pneumonia (PCP), or tuberculosis], which may necessitate further evaluation and treatment.

Autoimmune disorders (such as Graves' disease, polymyositis, Guillain-Barré syndrome, and autoimmune hepatitis) have also been reported to occur in the setting of immune reconstitution; however, the time to onset is more variable, and can occur many months after initiation of treatment.

5.2 Long-Acting Properties and Potential Associated Risks with SUNLENCA

Residual concentrations of lenacapavir may remain in the systemic circulation of patients for prolonged periods (up to 12 months or longer after the last subcutaneous dose). It is important to counsel patients that maintenance dosing by injection is required every 6 months, because missed doses or non-adherence to injections could lead to loss of virologic response and development of resistance [see Dosage and Administration (2.1)].

Lenacapavir, a moderate CYP3A inhibitor, may increase the exposure to, and therefore potential risk of adverse reactions from, drugs primarily metabolized by CYP3A initiated within 9 months after the last subcutaneous dose of SUNLENCA [see Drug Interactions and Clinical Pharmacology (7.2, 12.3)].

If SUNLENCA is discontinued, to minimize the potential risk of developing viral resistance, it is essential to initiate an alternative, fully suppressive antiretroviral regimen where possible no later than 28 weeks after the final injection of SUNLENCA. If virologic failure occurs during treatment, switch the patient to an alternative regimen if possible [see Dosage and Administration (2.1)].

5.3 Injection Site Reactions

Administration of SUNLENCA may result in local injection site reactions (ISRs). If clinically significant ISRs occur, evaluate and institute appropriate therapy and follow-up.

Manifestations of ISRs may include swelling, pain, erythema, nodule, induration, pruritus, extravasation or mass. Nodules and indurations at the injection site may take longer to resolve than other ISRs. In clinical studies, after a median follow-up of 553 days, 30% of nodules and 13% of indurations (in 10% and 1% of participants, respectively) associated with the first injections of SUNLENCA had not fully resolved. Measurements and qualitative assessments of ISRs were not routinely reported. Where described, the majority of the injection site nodules and indurations were palpable but not visible, and had a maximum size of approximately 1 to 4 cm [see Adverse Reactions (6.1)].

The mechanism driving the persistence of injection site nodules and indurations in some patients is not fully understood, but based on available data, they may be related to the presence of the subcutaneous drug depot. In some patients who had a skin biopsy performed of an injection site nodule or induration, dermatopathology revealed foreign body inflammation or granulomatous response.

Improper administration (intradermal injection) has been associated with serious injection site reactions, including necrosis and ulcer [see Adverse Reactions (6)]. Ensure SUNLENCA is only administered subcutaneously in the abdomen [see Dosage and Administration (2.4)].

6 ADVERSE REACTIONS

The following adverse reactions are discussed in other sections of the labeling:

- Immune Reconstitution Syndrome [see Warnings and Precautions (5.1)]
- Injection Site Reactions [see Warnings and Precautions (5.3)].

6.1 Clinical Trials Experience

Because clinical trials are conducted under widely varying conditions, adverse reaction rates observed in the clinical trials of a drug cannot be directly compared to rates in the clinical trials of another drug and may not reflect the rates observed in practice.

The primary safety assessment of SUNLENCA was based on data from heavily treatment-experienced adult participants with HIV who received SUNLENCA in a Phase 2/3 trial (CAPELLA; N=72) through Week 52 (median duration on study of 71 weeks) [see Clinical Studies (14)], as well as supportive data in treatment-naïve adult participants with HIV who received SUNLENCA in a Phase 2 trial (CALIBRATE; N=157) through Week 54 (median duration of exposure of 66 weeks).

The most common adverse reactions (all Grades) reported in at least 3% of participants in CAPELLA were nausea and injection site reactions. The proportion of partcipants in CAPELLA who discontinued treatment with SUNLENCA due to adverse events, regardless of severity, was 1% (Grade 1 injection site nodule in 1 participant). Table 3 displays the frequency of adverse reactions (all Grades) greater than or equal to 3% in the SUNLENCA group.

Table 3 Adverse Reactions (All Grades) Reported in ≥ 3% [Frequencies of adverse reactions are based on all adverse events attributed to trial drug by the investigator, based on all participants (cohorts 1 and 2) in CAPELLA.] of Heavily Treatment Experienced Adults with HIV-1 Receiving SUNLENCA in CAPELLA (Week 52 Analysis)
Adverse Reactions | SUNLENCA + Background Regimen (N=72)
Injection Site Reactions | 65%
Nausea | 4%

The majority (96%) of all adverse reactions associated with SUNLENCA were mild or moderate in severity.

Injection-Associated Adverse Reactions

Local Injection Site Reactions (ISRs):

The most frequent adverse reactions were ISRs. Of the 72 participants in CAPELLA, 65% had experienced an ISR attributed to study drug through at least the Week 52 visit. Most participants had mild (Grade 1, 44%) or moderate (Grade 2, 17%) ISRs. Four percent of participants experienced a severe (Grade 3) ISR (erythema, pain, swelling) that resolved within 15 days. The ISRs reported in more than 1% of participants were swelling (36%), pain (31%), erythema (31%), nodule (25%), induration (15%), pruritus (6%), extravasation (3%) and mass (3%). ISRs reported in 1% of participants included discomfort, hematoma, edema, and ulcer.

Nodules and indurations at the injection site took longer to resolve than other ISRs. The median time to resolution of all ISRs, excluding nodules and indurations, was 5 days (range: 1 to 183). The median time to resolution of nodules and indurations associated with the first injections of SUNLENCA was 148 (range: 41 to 727) and 70 (range: 3 to 252) days, respectively. After a median follow up of 553 days, 30% of nodules and 13% of indurations (in 10% and 1% of participants, respectively) associated with the first injections of SUNLENCA had not fully resolved. Qualitative descriptions of injection site nodules and indurations were not routinely reported, but, where reported, the majority of injection site nodules and indurations were palpable but not visible. Measurements of injection site nodules and indurations were not routinely performed or standardized, but where measurements were reported, the maximum size for the majority of injection site nodules and indurations was approximately 1 to 4 cm [see Warnings and Precautions (5.3)].

Laboratory Abnormalities

The frequency of laboratory abnormalities (Grades 3 to 4) occurring in at least 2% of participants in CAPELLA are presented in Table 4. A causal association between SUNLENCA and these laboratory abnormalities has not been established.

Table 4 Selected Laboratory Abnormalities (Grades 3 to 4) Reported in ≥ 2% of Participants Receiving SUNLENCA in CAPELLA (Week 52 Analysis)
Laboratory Parameter Abnormality | SUNLENCA + Background Regimen (N=72) [Frequencies are based on treatment-emergent laboratory abnormalities in all participants (cohorts 1 and 2) in CAPELLA. Percentages were calculated based on the number of participants with post-baseline toxicity grades for each laboratory parameter (n=72 for all parameters except hyperglycemia fasting n=57).]
Creatinine (>1.8 × ULN or ≥1.5 × baseline) | 13%
Glycosuria (>2+) [Grade 3 only (no Grade 4 values reported).] | 6%
Hyperglycemia (fasting) (>250 mg/dL) | 5%
Proteinuria (>2+) | 4%
ALT (≥5 × ULN) | 3%
AST (≥5 × ULN) | 3%
Direct Bilirubin (>ULN) | 3%
ALT= alanine aminotransferase; AST= aspartate aminotransferase; ULN = upper limit of normal

6.2 Postmarketing Experience

In addition to adverse reactions reported from clinical trials, the following adverse reactions have been identified during postmarketing use. Because these reactions are reported voluntarily from a population of uncertain size, it is not always possible to reliably estimate their frequency or establish a causal relationship to drug exposure.

General disorders and administration site conditions

Injection site necrosis [see Warnings and Precautions (5.3)].

7 DRUG INTERACTIONS

7.1 Effect of Other Drugs on SUNLENCA

Lenacapavir is a substrate of P-gp, UGT1A1, and CYP3A.

Strong or Moderate CYP3A Inducers

Drugs that are strong or moderate inducers of CYP3A may significantly decrease plasma concentrations of lenacapavir [see Clinical Pharmacology (12.3)], which may result in loss of therapeutic effect of SUNLENCA and development of resistance. Concomitant administration of SUNLENCA with strong CYP3A inducers during SUNLENCA treatment is contraindicated [see Contraindications (4)]. Concomitant administration of SUNLENCA with moderate CYP3A inducers during SUNLENCA treatment is not recommended.

Combined P-gp, UGT1A1, and Strong CYP3A Inhibitors

Combined P-gp, UGT1A1, and strong CYP3A inhibitors may significantly increase plasma concentrations of SUNLENCA. Concomitant administration of SUNLENCA with these inhibitors is not recommended.

7.2 Effect of SUNLENCA on Other Drugs

Lenacapavir is a moderate inhibitor of CYP3A. Due to the long half-life of lenacapavir following subcutaneous administration, SUNLENCA may increase the exposure of drugs primarily metabolized by CYP3A [see Clinical Pharmacology (12.3)] initiated within 9 months after the last subcutaneous dose of SUNLENCA, which may increase the potential risk of adverse reactions. See the prescribing information of the sensitive CYP3A substrate for dosing recommendations with moderate inhibitors of CYP3A.

7.3 Established and Other Potentially Significant Drug Interactions

Table 5 provides a listing of clinically significant drug interactions with recommended prevention or management strategies, but is not all inclusive. The drug interactions described are based on studies conducted with SUNLENCA or are drug interactions that may occur with SUNLENCA [see Contraindications (4) and Clinical Pharmacology (12.3)].

Table 5 Drug Interactions with SUNLENCA
Concomitant Drug Class: Drug Name | Effect on Concentration [↑ = Increase, ↓ = Decrease.] | Clinical Comment
Antiarrhythmics: digoxin | ↑ digoxin | Use with caution and monitor digoxin therapeutic concentration.
Anticoagulants: Direct Oral Anticoagulants (DOACs) rivaroxaban dabigatran edoxaban | ↑ DOAC | Refer to the DOAC prescribing information for concomitant administration with moderate CYP3A inhibitors and/or P-gp inhibitors.
Anticonvulsants: carbamazepine oxcarbazepine phenobarbital phenytoin | ↓ lenacapavir | Concomitant administration of carbamazepine, oxcarbazepine, phenobarbital, or phenytoin may result in loss of therapeutic effect and development of resistance. Concomitant administration of SUNLENCA with carbamazepine or phenytoin is contraindicated. Concomitant administration of SUNLENCA with oxcarbazepine or phenobarbital is not recommended. Consider use of alternative anticonvulsants.
Antiretroviral Agents: atazanavir/cobicistat [Drug-drug interaction study was conducted.] atazanavir/ritonavir | ↑ lenacapavir (atazanavir/cobicistat, atazanavir/ritonavir) | Concomitant administration of efavirenz, nevirapine, or tipranavir/ritonavir may result in loss of therapeutic effect and development of resistance.
efavirenz nevirapine tipranavir/ritonavir | ↓ lenacapavir (efavirenz, nevirapine, tipranavir/ritonavir) | Concomitant administration with atazanavir/cobicistat, atazanavir/ritonavir, efavirenz, nevirapine, or tipranavir/ritonavir is not recommended.
Antimycobacterials: rifabutin rifampin rifapentine | ↓ lenacapavir | Concomitant administration of rifabutin, rifampin and rifapentine may result in loss of therapeutic effect and development of resistance. Concomitant administration of SUNLENCA with rifampin is contraindicated [see Contraindications (4)]. Concomitant administration of SUNLENCA with rifabutin or rifapentine is not recommended.
Corticosteroids (systemic): cortisone/hydrocortisone dexamethasone | ↑ corticosteroids (systemic) | Concomitant administration with systemic corticosteroids whose exposures are significantly increased by CYP3A inhibitors can increase the risk for Cushing's syndrome and adrenal suppression. Initiate with the lowest starting dose and titrate carefully while monitoring for safety.
 | ↓ lenacapavir (dexamethasone) | Concomitant administration of systemic dexamethasone may result in loss of therapeutic effect of lenacapavir and development of resistance. Alternative corticosteroids to dexamethasone should be considered, particularly for long-term use.
Ergot derivatives: dihydroergotamine ergotamine methylergonovine | ↑ dihydroergotamine ↑ ergotamine ↑ methylergonovine | Concomitant administration of SUNLENCA with dihydroergotamine, ergotamine or methylergonovine is not recommended.
Herbal Products: St. John's wort [The induction potency of St. John's wort may vary widely based on preparation.] (Hypericum perforatum) | ↓ lenacapavir | Concomitant administration of St. John's wort may result in loss of therapeutic effect and development of resistance. Concomitant administration of SUNLENCA with St. John's wort is contraindicated.
HMG-CoA Reductase Inhibitors: lovastatin simvastatin | ↑ lovastatin ↑ simvastatin | Initiate lovastatin and simvastatin with the lowest starting dose and titrate carefully while monitoring for safety (e.g., myopathy).
Narcotic analgesics metabolized by CYP3A: e.g., fentanyl, oxycodone | ↑ fentanyl ↑ oxycodone | Careful monitoring of therapeutic effects and adverse reactions associated with CYP3A-metabolized narcotic analgesics (including potentially fatal respiratory depression) is recommended with co-administration.
tramadol | ↑ tramadol | A decrease in dose may be needed for tramadol with concomitant use.
Narcotic analgesic for treatment of opioid dependence: buprenorphine, methadone | buprenorphine: effects unknown methadone: effects unknown | Initiation of buprenorphine or methadone in patients taking SUNLENCA: Carefully titrate the dose of buprenorphine or methadone to the desired effect; use the lowest feasible initial or maintenance dose. Initiation of SUNLENCA in patients taking buprenorphine or methadone: A dose adjustment for buprenorphine or methadone may be needed. Monitor clinical signs and symptoms.
Opioid Antagonist: naloxegol | ↑ naloxegol | Avoid use with SUNLENCA; if unavoidable, decrease the dosage of naloxegol and monitor for adverse reactions.
Phosphodiesterase-5 (PDE-5) Inhibitors: sildenafil tadalafil vardenafil | ↑ PDE-5 inhibitors | Use of PDE-5 inhibitors for pulmonary arterial hypertension (PAH): Concomitant administration of SUNLENCA with tadalafil for the treatment of PAH is not recommended. Use of PDE-5 inhibitors for erectile dysfunction (ED): Refer to the prescribing information of PDE-5 inhibitors for dose recommendations.
Sedatives/Hypnotics: midazolam (oral) triazolam | ↑ midazolam (oral) ↑ triazolam | Use with caution when midazolam or triazolam is concomitantly administered with SUNLENCA

7.4 Drugs without Clinically Significant Interactions with SUNLENCA

Based on drug interaction studies conducted with SUNLENCA, no clinically significant drug interactions have been observed with: darunavir/cobicistat, cobicistat, famotidine, pitavastatin, rosuvastatin, tenofovir alafenamide, and voriconazole.

8 USE IN SPECIFIC POPULATIONS

8.1 Pregnancy

Pregnancy Exposure Registry

There is a pregnancy exposure registry that monitors pregnancy outcomes in individuals exposed to SUNLENCA during pregnancy. Healthcare providers are encouraged to register patients by calling the Antiretroviral Pregnancy Registry (APR) at 1-800-258-4263.

Risk Summary

There are insufficient human data on the use of SUNLENCA during pregnancy to inform a drug-associated risk of birth defects and miscarriage. In animal reproduction studies, no adverse developmental effects were observed when lenacapavir was administered to rats and rabbits at exposures (AUC) ≥16 times the exposure in humans at the recommended human dose (RHD) of SUNLENCA (see Data).

The background risk of major birth defects and miscarriage for the indicated population is unknown. The background rate of major birth defects in a U.S. reference population of the Metropolitan Atlanta Congenital Defects Program (MACDP) is 2.7%. The rate of miscarriage is not reported in the APR. The estimated background rate of miscarriage in clinically recognized pregnancies in the U.S. general population is 15 to 20%.

Data

Animal Data

Lenacapavir was administered intravenously to pregnant rabbits (up to 20 mg/kg/day on gestation days (GD) 7 to 19), orally to rats (up to 300 mg/kg/day on GD 6 to 17), and subcutaneously to rats (up to 300 mg/kg on GD 6). No significant toxicological effects on embryo-fetal (rats and rabbits) or pre/postnatal (rats) development were observed at exposures (AUC) approximately 16 times (rats) and 39 times (rabbits) the exposure in humans at the RHD of SUNLENCA.

8.2 Lactation

Risk Summary

It is not known whether SUNLENCA is present in human breast milk, affects human milk production, or has effects on the breastfed infant. After administration to pregnant rats, lenacapavir was detected in the plasma of nursing rat pups, without effects on these nursing pups (see Data).

Potential risks of breastfeeding include: (1) HIV-1 transmission (in infants without HIV-1), (2) developing viral resistance (in infants with HIV-1), and (3) adverse reactions in a breastfed infant similar to those seen in adults.

Data

Lenacapavir was detected at low levels in the plasma of nursing rat pups in the pre/postnatal development study (post-natal day 10).

8.4 Pediatric Use

The safety and effectiveness of SUNLENCA have not been established in pediatric patients.

8.5 Geriatric Use

Clinical studies of SUNLENCA did not include sufficient numbers of participants aged 65 and over to determine whether they respond differently from younger patients.

8.6 Renal Impairment

No dosage adjustment of SUNLENCA is recommended in patients with mild, moderate or severe renal impairment (estimated creatinine clearance greater than or equal to 15 mL per minute). SUNLENCA has not been studied in patients with ESRD (estimated creatinine clearance less than 15 mL per minute) [see Clinical Pharmacology (12.3)].

8.7 Hepatic Impairment

No dosage adjustment of SUNLENCA is recommended in patients with mild (Child-Pugh Class A) or moderate (Child-Pugh Class B) hepatic impairment. SUNLENCA has not been studied in patients with severe hepatic impairment (Child-Pugh Class C) [see Clinical Pharmacology (12.3)].

10 OVERDOSAGE

No data are available on overdose of SUNLENCA in patients. If overdose occurs, monitor the patient for evidence of toxicity. Treatment of overdose with SUNLENCA consists of general supportive measures including monitoring of vital signs as well as observation of the clinical status of the patient. As lenacapavir is highly bound to plasma proteins, it is unlikely to be significantly removed by dialysis.

11 DESCRIPTION

SUNLENCA tablets and SUNLENCA injection contain lenacapavir sodium, a capsid inhibitor.

The chemical name of lenacapavir sodium is: Sodium (4-chloro-7-(2-((S)-1-(2-((3bS,4aR)-5,5-difluoro-3-(trifluoromethyl)-3b,4,4a,5-tetrahydro-1H-cyclopropa[3,4]cyclopenta[1,2-c]pyrazol-1-yl)acetamido)-2-(3,5-difluorophenyl)ethyl)-6-(3-methyl-3-(methylsulfonyl)but-1-yn-1-yl)pyridin-3-yl)-1-(2,2,2-trifluoroethyl)-1H-indazol-3-yl)(methylsulfonyl)amide.

Lenacapavir sodium has a molecular formula of C39H31ClF10N7NaO5S2, a molecular weight of 990.3, and the following structural formula:

Lenacapavir sodium is a light yellow to yellow solid and is practically insoluble in water.

SUNLENCA tablets are for oral administration. Each film-coated tablet contains 300 mg of lenacapavir (present as 306.8 mg lenacapavir sodium) and the following inactive ingredients: copovidone, croscarmellose sodium, magnesium stearate, mannitol, microcrystalline cellulose, and poloxamer 407. The tablets are film-coated with a coating material containing iron oxide black, iron oxide red, iron oxide yellow, polyethylene glycol, polyvinyl alcohol, talc, and titanium dioxide.

SUNLENCA injection is for subcutaneous administration. Each single-dose vial contains 463.5 mg/1.5 mL (309 mg/mL) of lenacapavir (present as 473.1 mg/1.5 mL of lenacapavir sodium) as a sterile, preservative-free, clear, yellow solution and the following inactive ingredients: 896.3 mg of polyethylene glycol 300 (as solvent) and water for injection. The apparent pH range of the injection is 9.0–10.2.

The vial stoppers are not made with natural rubber latex.

12 CLINICAL PHARMACOLOGY

12.1 Mechanism of Action

SUNLENCA is an HIV-1 antiretroviral agent [see Microbiology (12.4)].

12.2 Pharmacodynamics

Exposure-Response

In CAPELLA, oral loading doses (600 mg on Day 1 and Day 2, 300 mg on Day 8) followed by subcutaneous doses (927 mg every 6 months starting on Day 15) of SUNLENCA in heavily treatment-experienced participants with multiclass resistant HIV-1, efficacy outcomes (change in plasma HIV-1 RNA from Day 1 to Day 14, and percentage of participants with HIV-1 RNA less than 50 copies/mL at Week 26) were similar across the range of observed lenacapavir exposures.

Cardiac Electrophysiology

At supratherapeutic exposures of lenacapavir (9-fold higher than the therapeutic exposures of SUNLENCA), SUNLENCA does not prolong the QTcF interval to any clinically relevant extent.

12.3 Pharmacokinetics

The pharmacokinetic (PK) properties of lenacapavir are provided in Table 6 and Table 7. The estimated lenacapavir exposures are comparable between the two recommended dosing regimens.

Table 6 Pharmacokinetic Properties of Lenacapavir
 |  | Oral | Subcutaneous
Absorption
% Absolute bioavailability |  | 6 to 10 | 100 [Values reflect absolute bioavailability following subcutaneous administration of the 927 mg dose.]
Tmax [Values reflect administration of lenacapavir with or without food.] |  | 4 hours | 77 to 84 days [Due to slow release from the site of subcutaneous administration, the absorption profile of subcutaneously administered lenacapavir is complex.]
Effect of Food
Effect of low-fat meal (relative to fasting) [Values refer to geometric mean ratio [low-fat meal/fasting] in PK parameters and (90% confidence interval). Low fat meal is approximately 400 kcal, 25% fat.] | AUCinf ratio | 98.6 (58.2,167.2) | -
Effect of low-fat meal (relative to fasting) [Values refer to geometric mean ratio [low-fat meal/fasting] in PK parameters and (90% confidence interval). Low fat meal is approximately 400 kcal, 25% fat.] | Cmax ratio | 115.8 (55.4, 242.1) | -
Effect of high-fat meal (relative to fasting) [Values refer to geometric mean ratio [high-fat meal/fasting] in PK parameters and (90% confidence interval). High fat meal is approximately 1000 kcal, 50% fat.] | AUCinf ratio | 115.2 (72.0, 184.5) | -
Effect of high-fat meal (relative to fasting) [Values refer to geometric mean ratio [high-fat meal/fasting] in PK parameters and (90% confidence interval). High fat meal is approximately 1000 kcal, 50% fat.] | Cmax ratio | 145.2 (77.9, 270.5) | -
Distribution
Apparent volume of distribution (Vd/F, L) |  | 19240 | 9500 to 11700
% bound to human plasma proteins |  | >98.5
Blood-to-plasma ratio |  | 0.5 to 0.7 [Values reflect the blood-to-plasma ratio of lenacapavir following a single dose intravenous administration of [^14C] lenacapavir through 336 hours postdose.]
Elimination
t1/2 |  | 10 to 12 days | 8 to 12 weeks
Clearance (mean apparent clearance, L/h) |  | 55 | 4.2
% of dose of unchanged drug in plasma [Dosing in mass balance studies: single dose intravenous administration of [^14C] lenacapair to participants without HIV-1.] |  | 69
Metabolism
Metabolic pathway(s) |  | CYP3A (minor) UGT1A1 (minor)
Excretion
Major routes of elimination |  | Excretion of unchanged drug into feces [Metabolized via oxidation, N-dealkylation, hydrogenation, amide hydrolysis, glucuronidation, hexose conjugation, pentose conjugation, and glutathione conjugation; primarily via CYP3A and UGT1A1 and no single circulating metabolite accounted for >10% of plasma drug-related exposure.]
% of dose excreted in urine |  | <1
% of dose excreted in feces (% unchanged) |  | 76 (33)

Table 7 Lenacapavir Exposures Following Oral and Subcutaneous Administration of SUNLENCA in Heavily Treatment Experienced Participants with HIV
Parameter Mean (%CV) | Recommended Dosing Regimen, Option 1 [Predicted exposures utilizing population PK analysis.] | Recommended Dosing Regimen, Option 2
Parameter Mean (%CV) | Day 1: 600 mg (oral) + 927 mg (SC) Day 2: 600 mg (oral) | Days 1 and 2: 600 mg (oral), Day 8: 300 mg (oral), Day 15: 927 mg (SC)
Parameter Mean (%CV) | Day 1 to end of Month 6 | Days 1 to 15 | Day 15 to end of Month 6
Cmax (ng/mL) | 101.4 (53.1) | 88.0 (72.4) | 86.5 (51.7)
AUCtau (h∙ng/mL) | 242266 (46.0) | 19496 (72.6) | 239163 (47.2)
Ctrough (ng/mL) | 32.5 (57.2) | 46.9 (72.3) | 32.5 (57.5)
CV = coefficient of variation; NA = not applicable; SC = subcutaneous

Lenacapavir exposures after subcutaneous administration were similar between heavily treatment experienced participants with HIV-1 and participants without HIV-1 based on population pharmacokinetics analysis. Lenacapavir exposures (AUCtau, Cmax and Ctrough) after oral administration were 28% to 43% higher in participants with HIV-1 who were heavily treatment experienced, compared to participants without HIV-1 based on population PK analysis. These differences were not considered clinically relevant.

Specific Populations

There were no clinically significant differences in the pharmacokinetics of lenacapavir based on age (18 to 78 years), sex, ethnicity (hispanic or non-hispanic), race (white, black, asian or other), body weight (41.4 to 164 kg), severe renal impairment (creatinine clearance of 15 to less than 30 mL per minute, estimated by Cockroft-Gault method), or moderate hepatic impairment (Child-Pugh Class B). The effect of end-stage renal disease (including dialysis), or severe hepatic impairment (Child-Pugh Class C), on the pharmacokinetics of lenacapavir is unknown. As lenacapavir is greater than 98.5% protein bound, dialysis is not expected to alter exposures of lenacapavir [see Use in Specific Populations (8.6)].

Drug Interaction Studies

Clinical Studies

Clinical drug-drug interaction study indicated that lenacapavir is a substrate of CYP3A, P-gp, and UGT1A1. Table 8 summarizes the pharmacokinetic effects of other drugs on lenacapavir.

Lenacapavir is a moderate inhibitor of CYP3A. Lenacapavir is an inhibitor of P-gp and BCRP but does not inhibit OATP. Table 9 summarizes the pharmacokinetic effects of lenacapavir on other drugs.

Table 8 Effect of Other Drugs on Lenacapavir [Single dose of lenacapavir 300 mg administered orally.] , [All interaction studies conducted in participants without HIV-1.]
Coadministered Drug | Dose of Coadministered Drug (mg) | Mean Ratio of Lenacapavir Pharmacokinetic Parameters (90% CI); No effect = 1.00
Coadministered Drug | Dose of Coadministered Drug (mg) | Cmax | AUC
Cobicistat (fed) (Inhibitor of CYP3A [strong] and P-gp) | 150 once daily | 2.10 (1.62, 2.72) | 2.28 (1.75, 2.96)
Darunavir / cobicistat (fed) (Inhibitor of CYP3A [strong] and inhibitor and inducer of P-gp) | 800/150 once daily | 2.30 (1.79, 2.95) | 1.94 (1.50, 2.52)
Voriconazole (fasted) (Inhibitor of CYP3A [strong]) | 400 twice daily, 200 twice daily [400 mg loading dose twice daily for a day, followed by 200 mg maintenance dose twice daily.] | 1.09 (0.81, 1.47) | 1.41 (1.10, 1.81)
Atazanavir / cobicistat (fed) (Inhibitor of CYP3A [strong] and UGT1A1 and P-gp) | 300/150 once daily | 6.60 (4.99, 8.73) | 4.21 (3.19, 5.57)
Rifampin (fasted) (Inducer of CYP3A [strong] and P-gp and UGT) | 600 once daily | 0.45 (0.34, 0.60) | 0.16 (0.12, 0.20)
Efavirenz (fasted) (Inducer of CYP3A [moderate] and P-gp) | 600 once daily | 0.64 (0.45, 0.92) | 0.44 (0.32, 0.59)
Famotidine (2 hours before, fasted) | 40 once daily | 1.01 (0.75, 1.34) | 1.28 (1.00, 1.63)

Table 9 Effect of Lenacapavir on Other Drugs [All interaction studies conducted in participants without HIV-1.] , [Following 600 mg twice daily for 2 days, single 600 mg doses of lenacapavir were administered with each coadministered drug, resulting in lenacapavir exposures similar to or higher than those at the recommended dosage regimen.]
Coadministered Drug | Dose of Coadministered Drug (mg) | Mean Ratio of Coadministered Drug Pharmacokinetic Parameters (90% CI) [All No Effect Boundaries are 70% to 143%.] ; No effect = 1.00
Coadministered Drug | Dose of Coadministered Drug (mg) | Cmax | AUC
Tenofovir alafenamide (fed) (substrate of P-gp) | 25 single dose | 1.24 (0.98, 1.58) | 1.32 (1.09, 1.59)
Tenofovir [Tenofovir alafenamide is converted to tenofovir in vivo.] (substrate of P-gp) |  | 1.23 (1.05, 1.44) | 1.47 (1.27, 1.71)
Pitavastatin (simultaneous administration, fed) (substrate of OATP) | 2 single dose | 1.00 (0.84, 1.19) | 1.11 (1.00, 1.25)
Pitavastatin (3 days after lenacapavir, fed) (substrate of OATP) | 2 single dose | 0.85 (0.69, 1.05) | 0.96 (0.87, 1.07)
Rosuvastatin (fed) (substrate of BCRP and OATP) | 5 single dose | 1.57 (1.38, 1.80) | 1.31 (1.19, 1.43)
Midazolam (simultaneous administration, fed) (substrate of CYP3A) | 2.5 single dose | 1.94 (1.81, 2.08) | 3.59 (3.30, 3.91)
1-hydroxymidazolam [Major active metabolite of midazolam.] (substrate of CYP3A) |  | 0.54 (0.50, 0.59) | 0.76 (0.72, 0.80)
Midazolam (1 day after lenacapavir, fed) (substrate of CYP3A) | 2.5 single dose | 2.16 (2.02, 2.30) | 4.08 (3.77, 4.41)
1-hydroxymidazolam (substrate of CYP3A) |  | 0.52 (0.48, 0.57) | 0.84 (0.80, 0.88)

In Vitro Studies

Cytochrome P450 (CYP) Enzymes: Lenacapavir is not a substrate, inducer, or inhibitor of CYP1A2, CYP2B6, CYP2C8, CYP2C9, CYP2C19, and CYP2D6. Lenacapavir is not an inducer of CYP3A4.

Uridine diphosphate (UDP)-glucuronosyl transferase (UGT) Enzymes: Lenacapavir is not an inhibitor of UGT1A1.

Transporter Systems: Lenacapavir is not an inhibitor of organic anion transporter 1 (OAT1), OAT3, organic cation transporter (OCT)1, OCT2, multidrug and toxin extrusion transporter (MATE) 1, or MATE 2-K. Lenacapavir is not a substrate of BCRP, OATP1B1, or OATP1B3.

12.4 Microbiology

Mechanism of Action

Lenacapavir is a multistage, selective inhibitor of HIV-1 capsid function that directly binds to the interface between capsid protein (p24) subunits in hexamers. Surface plasmon resonance sensorgrams showed dose-dependent and saturable binding of lenacapavir to cross-linked wild-type capsid hexamer with an equilibrium binding constant (KD) of 1.4 nM. Lenacapavir inhibits HIV-1 replication by interfering with multiple essential steps of the viral lifecycle, including capsid-mediated nuclear uptake of HIV-1 proviral DNA (by blocking nuclear import proteins binding to capsid), virus assembly and release (by interfering with Gag/Gag-Pol functioning, reducing production of capsid protein subunits), and capsid core formation (by disrupting the rate of capsid subunit association, leading to malformed capsids).

Antiviral Activity in Cell Culture

Lenacapavir has antiviral activity that is specific to human immunodeficiency virus (HIV-1 and HIV-2). The antiviral activity of lenacapavir against laboratory and clinical isolates of HIV-1 was assessed in T-lymphoblastoid cell lines, PBMCs, primary monocyte/macrophage cells, and CD4^+ T-lymphocytes with EC50 values ranging from 30 to 190 pM. Lenacapavir displayed antiviral activity in cell culture against all HIV-1 groups (M, N, O), including subtypes A, A1, AE, AG, B, BF, C, D, E, F, G with EC50 values ranging from 20 and 160 pM. The median EC50 value for subtype B isolates (n=8) was 40 pM. Lenacapavir was 15- to 25-fold less active against HIV-2 isolates relative to HIV-1.

In a study of lenacapavir in combination with representatives from the major classes of anti-retroviral agents (INSTIs, NNRTIs, NRTIs, and PIs), no antagonism of antiviral activity was observed.

Resistance

In Cell Culture

HIV-1 variants with reduced susceptibility to lenacapavir have been selected in cell culture. Resistance selections with lenacapavir identified 7 substitutions in capsid: L56I, M66I, Q67H, K70N, N74D/S, and T107N singly or in dual combination that conferred 4- to >3,226-fold reduced phenotypic susceptibility to lenacapavir relative to wild-type (WT) virus. The M66I substitution alone or in combination conferred >3,226-fold decreased susceptibility to lenacapavir in a single-cycle infectivity assay; substitutions Q67H and T107N, conferred 4- to 6.3-fold decreased susceptibility; K70N, N74D and Q67H/N74S conferred 22- to 32-fold decreased susceptibility; and L56I conferred 239-fold decreased susceptibility.

In Clinical Trials

In CAPELLA, 31% (22/72) of heavily treatment-experienced participants met the criteria for resistance analyses through Week 52 (HIV-1 RNA ≥ 50 copies/mL at confirmed virologic failure [suboptimal virologic response at Week 4, virologic rebound, or viremia at last visit]) and were analyzed for lenacapavir resistance-associated substitution emergence. Lenacapavir resistance-associated capsid substitutions were found in 41% (n=9) of participants with confirmed virologic failure who had post-baseline capsid genotypic resistance data (n=22). The M66I capsid substitution was observed in 27% (6/22) of participants, alone or in combination with other lenacapavir resistance-associated capsid substitutions including Q67Q/H, Q67Q/H/K/N, K70K/R, K70N/S, N74D, N74N/H, A105T, and T107A. The other 3 participants with virologic failure had emergent lenacapavir resistance-associated capsid substitutions Q67K+K70H, Q67H+K70R+T107S, and Q67Q/H.

Phenotypic analyses of the confirmed virologic failure isolates with emergent lenacapavir resistance-associated substitutions showed 6- to >1428-fold decreases in lenacapavir susceptibility when compared to WT.

Among the 9 participants with virologic failure who developed lenacapavir resistance-associated substitutions in capsid, 4 received SUNLENCA in combination with a background regimen with no fully active antiretrovirals based on the baseline genotypic and/or phenotypic resistance. Therefore, given the risk of developing resistance in situations of functional monotherapy, careful consideration should be given to having active drugs in addition to SUNLENCA in the treatment regimen.

Four participants with virologic failure had emergent resistance substitutions to components of the optimized background regimen (OBR): emergent NRTI substitution M184I/V and NNRTI substitution K103N/Y with emtricitabine and doravirine plus atazanavir, bictegravir, and tenofovir alafenamide in OBR; emergent NNRTI substitution V106M from a mixture at baseline (in addition to lenacapavir resistance-associated substitutions M66I + T107A) with doravirine plus emtricitabine and ibalizumab in OBR; emergent NRTI substitutions K65R and S68N from mixtures at baseline (in addition to lenacapavir resistance-associated substitution M66I) with tenofovir alafenamide, plus emtricitabine, dolutegravir, darunavir/cobicistat, and rilpivirine in OBR; and emergent NRTI substitution K65K/R with tenofovir disoproxil fumarate plus darunavir/cobicistat, dolutegravir, and emtricitabine in OBR.

Oral Maintenance for Missed Injections

Of the 57 participants who received oral maintenance, 9 participants (5 participants in Cohort 1 and 4 participants in Cohort 2) met the criteria for resistance analysis. Six of these 9 participants had emergent lenacapavir resistance substitutions in capsid (Q67H [n=4], K70R or N [n=2], N74D or K [n=2], T107N [n=1]) with 4.5- to 393-fold decreased lenacapavir susceptibility. In addition, 2 participants had emergent resistance substitutions to darunavir in their optimized background regimen.

Lenacapavir Resistance with Suboptimal Adherence to Other Antiretroviral Drugs in the Regimen

The development of lenacapavir-associated capsid resistance substitutions in 6 participants during the oral maintenance period was likely due to suboptimal adherence to the optimized background oral regimens that included dolutegravir and/or darunavir. After developing lenacapavir resistance, 5 of the 6 participants achieved HIV-1 RNA resuppression (HIV-1 RNA < 50 copies/mL) while maintaining SUNLENCA treatment. With the emergence of lenacapavir resistance substitutions and decreased susceptibility to lenacapavir, it is unclear how much antiviral activity lenacapavir is contributing to the resuppression of HIV-1 RNA in these 5 participants.

Thus, adherence to other antiretroviral drugs in the regimen should be optimized while the patient is receiving SUNLENCA. During SUNLENCA treatment, if suboptimal adherence to the oral antiretroviral regimen occurs with concurrent HIV-1 RNA viral load increases (i.e., virologic failure), lenacapavir resistance should be assessed, and if detected, consideration should be given to discontinuing SUNLENCA treatment [see Dosage and Administration (2.1), Warnings and Precautions (5.2)].

Cross-Resistance

The antiviral activity in cell culture of lenacapavir was determined against a broad spectrum of HIV-1 site-directed mutants and patient-derived HIV-1 isolates with resistance to the four main classes of anti-retroviral agents (INSTI, NNRTI, NRTI, and PI; n=58), as well as to viruses resistant to the gp120-directed attachment inhibitor fostemsavir, the CD4^+-directed post-attachment inhibitor ibalizumab, the CCR5 co-receptor antagonist maraviroc, and the gp41 fusion inhibitor enfuvirtide (n=42). These data indicated that lenacapavir remained fully active against all variants tested, thereby demonstrating a non-overlapping resistance profile. In addition, the antiviral activity of lenacapavir in patient isolates was unaffected by the presence of naturally occurring Gag polymorphisms and substitutions at protease cleavage sites.

13 NONCLINICAL TOXICOLOGY

13.1 Carcinogenesis, Mutagenesis, Impairment of Fertility

Carcinogenesis

Lenacapavir was not carcinogenic in a 6-month rasH2 transgenic mouse study in males or females at doses of up to 300 mg/kg/dose once every 13 weeks.

A 104-week carcinogenicity study was conducted in male and female rats at lenacapavir doses of 0, 102, 309, or 927 mg/kg by subcutaneous injection once every 13-weeks. A treatment-related increase in the incidence of malignant sarcoma at the injection site was observed in males and a treatment-related increase in combined benign fibroma and malignant fibrosarcoma at the injection site was observed in females, at the highest dose (927 mg/kg). This dose in rats resulted in an exposure approximately 34-times the human exposure at the RHD, based on AUC. These tumors are considered to be a secondary response to chronic tissue irritation and granulomatous inflammation, due to the depot effect of lenacapavir following subcutaneous injection. The clinical relevance of these findings are unknown.

Mutagenesis

Lenacapavir was not mutagenic in a battery of in vitro and in vivo genotoxicity assays, including microbial mutagenesis, chromosome aberration in human peripheral blood lymphocytes, and in in vivo rat micronucleus assays.

Impairment of Fertility

There were no effects on fertility, mating performance or early embryonic development when lenacapavir was administered to rats at systemic exposures (AUC) 5 times the exposure to humans at the RHD of SUNLENCA.

14 CLINICAL STUDIES

The efficacy and safety of SUNLENCA in heavily treatment-experienced participants with multidrug resistant HIV-1 is based on 52-week data from CAPELLA, a randomized, placebo-controlled, double-blind, multicenter trial (NCT 04150068).

CAPELLA was conducted in 72 heavily treatment-experienced participants with multiclass resistant HIV-1. Participants were required to have a viral load ≥ 400 copies/mL, documented resistance to at least two antiretroviral medications from each of at least 3 of the 4 classes of antiretroviral medications (NRTI, NNRTI, PI and INSTI), and ≤ 2 fully active antiretroviral medications from the 4 classes of antiretroviral medications remaining at baseline due to resistance, intolerability, drug access, contraindication, or other safety concerns.

The trial was composed of two cohorts. Participants were enrolled into the randomized cohort (cohort 1, N=36) if they had a < 0.5 log10 HIV-1 RNA decline compared to the screening visit. Participants were enrolled into the non-randomized cohort (cohort 2, N=36) if they had a ≥ 0.5 log10 HIV-1 RNA decline compared to the screening visit or after cohort 1 reached its planned sample size.

In the 14-day functional monotherapy period, participants in cohort 1 were randomized in a 2:1 ratio in a blinded fashion to receive either SUNLENCA or placebo, while continuing their failing regimen. This period was to establish the virologic activity of SUNLENCA. After the functional monotherapy period, participants who had received SUNLENCA continued on SUNLENCA along with an optimized background regimen (OBR); participants who had received placebo during this period initiated SUNLENCA along with an OBR.

Participants in cohort 1 had a mean age of 52 years (range: 24 to 71), 72% were male, 46% were White, 46% were Black, and 9% were Asian. 29% percent of participants identified as Hispanic/Latino. The mean baseline plasma HIV-1 RNA was 4.3 log10 copies/mL (range: 2.3 to 5.4). 19% of participants had baseline viral loads greater than 100,000 copies/mL. The mean baseline CD4^+ cell count was 161 cells/mm^3 (range: 6 to 827). 75% of participants had CD4^+ cell counts below 200 cells/mm^3. The mean number of years since participants first started HIV treatment was 24 years (range: 7 to 33); the mean number of antiretroviral agents in failing regimens at baseline was 4 (range: 1 to 7). The percentage of participants in the randomized cohort with known resistance to at least 2 agents from the NRTI, NNRTI, PI and INSTI classes was 97%, 94%, 78% and 75%, respectively. In cohort 1, 53% of participants had no fully active agents, 31% had 1 fully active agent, and 17% had 2 or more fully active agents within their initial failing regimen, including 6% of participants were who were receiving fostemsavir, which was an investigational agent at the start of the CAPELLA trial.

Participants in cohort 2 initiated SUNLENCA and an OBR on Day 1.

Participants in cohort 2 had a mean age of 48 years (range: 23 to 78), 78% were male, 36% were White, 31% were Black, 33% were Asian, and 14% of participants identified as Hispanic/Latino. The mean baseline plasma HIV-1 RNA was 4.1 log10 copies/mL (range: 1.3 to 5.7). 19% of participants had baseline viral loads greater than 100,000 copies/mL. The mean baseline CD4^+ cell count was 258 cells/mm^3 (range: 3 to 1296). 53% of participants had CD4^+ cell counts below 200 cells/mm^3. The mean number of years since participants first started HIV treatment was 19 years (range: 3 to 35); the mean number of antiretroviral agents in failing regimens at baseline was 4 (range: 2 to 7). The percentage of participants in the non-randomized cohort with known resistance to at least 2 agents from the NRTI, NNRTI, PI and INSTI classes was 100%, 100%, 83% and 64%, respectively. In cohort 2, 31% of participants had no fully active agents, 42% had 1 fully active agent, and 28% had 2 or more fully active agents within their initial failing regimen, including 6% of participants who were receiving fostemsavir, which was an investigational agent at the start of the CAPELLA trial.

The primary efficacy endpoint was the proportion of participants in cohort 1 achieving ≥ 0.5 log10 copies/mL reduction from baseline in HIV-1 RNA at the end of the functional monotherapy period. The results of the primary endpoint analysis are shown in Table 10.

Table 10 Proportion of Participants Achieving a ≥ 0.5 log10 Decrease in Viral Load at the End of the Functional Monotherapy Period in the CAPELLA Trial (Cohort 1)
 | SUNLENCA (N=24) | Placebo (N=12)
Proportion of Participants Achieving a ≥ 0.5 log10 Decrease in Viral Load | 87.5% | 16.7%
Treatment Difference (95% CI) | 70.8% (34.9% to 90.0%) [p < 0.0001]

The results at Weeks 26 and 52 are provided in Table 11 and Table 12.

Table 11 Virologic Outcomes (HIV-1 RNA < 50 copies/mL) at Weeks 26 [Week 26 window was between Days 184 and 232 (inclusive).] and 52 [Week 52 window was between Days 324 and 414 (inclusive).] with SUNLENCA plus OBR in the CAPELLA Trial (Cohort 1)
 | SUNLENCA plus OBR (N=36)
 | Week 26 | Week 52
HIV-1 RNA < 50 copies/mL | 81% | 83%
HIV-1 RNA ≥ 50 copies/mL [Includes participants who had ≥ 50 copies/mL in the Week 26 or 52 window; participant who discontinued early due to lack or loss of efficacy; participants who discontinued for reasons other than an adverse event (AE), death or lack or loss of efficacy and at the time of discontinuation had a viral value of ≥ 50 copies/mL.] | 19% | 14%
No virologic data in Week 26 or 52 Window | 0 | 3%
Discontinued Study Drug Due to AE or Death [Includes participants who discontinued due to AE or death at any time point from Day 1 through the time window if this resulted in no virologic data on treatment during the specified window.] | 0 | 0
Discontinued Study Drug Due to Other Reasons [Includes participants who discontinued for reasons other than an AE, death or lack or loss of efficacy, e.g., withdrew consent, loss to follow-up, etc.] and Last Available HIV-1 RNA < 50 copies/mL | 0 | 3%
Missing Data During Window but on Study Drug | 0 | 0
OBR = optimized background regimen

Table 12 Virologic Outcomes (HIV-1 RNA < 50 copies/mL) by Baseline Covariates at Weeks 26 [Week 26 window was between Days 184 and 232 (inclusive).] and 52 [Week 52 window was between Days 324 and 414 (inclusive).] with SUNLENCA plus OBR in the CAPELLA trial (Cohort 1)
 | SUNLENCA plus OBR (N=36)
 | Week 26 | Week 52
Age (Years)
< 50 | 100% (9/9) | 89% (8/9)
≥ 50 | 74% (20/27) | 81% (22/27)
Gender
Male | 77% (20/26) | 77% (20/26)
Female | 90% (9/10) | 100% (10/10)
Race
Black | 81% (13/16) | 75% (12/16)
Non-Black | 84% (16/19) | 89% (17/19)
Baseline plasma viral load (copies/mL)
≤ 100,000 | 86% (25/29) | 86% (25/29)
> 100,000 | 57% (4/7) | 71% (5/7)
Baseline CD4^+ (cells/mm^3)
< 200 | 78% (21/27) | 78% (21/27)
≥ 200 | 89% (8/9) | 100% (9/9)
Baseline INSTI resistance profile
With INSTI resistance | 85% (23/27) | 81% (22/27)
Without INSTI resistance | 63% (5/8) | 88% (7/8)
Number of fully active ARV agents in the OBR
0 | 67% (4/6) | 67% (4/6)
1 | 86% (12/14) | 79% (11/14)
≥ 2 | 81% (13/16) | 94% (15/16)
Use of DTG and/or DRV in the OBR
With DTG and DRV | 83% (10/12) | 83% (10/12)
With DTG, without DRV | 83% (5/6) | 83% (5/6)
Without DTG, with DRV | 78% (7/9) | 89% (8/9)
Without DTG or DRV | 78% (7/9) | 78% (7/9)
ARV = antiretroviral; DRV=darunavir; DTG=dolutegravir; INSTI = integrase strand-transfer inhibitor; OBR = optimized background regimen;

In cohort 1, at Weeks 26 and 52, the mean change from baseline in CD4^+ cell count was 81 cells/mm^3 (range: -101 to 522) and 82 cells/mm^3 (range: -194 to 467), respectively.

In cohort 2, at Weeks 26 and 52, 81% (29/36) and 72% (26/36) of participants achieved HIV-1 RNA < 50 copies/mL, respectively, and the mean change from baseline in CD4^+ cell count was 97 cells/mm^3 (range: -103 to 459) and 113 cells/mm^3 (range: -124 to 405), respectively.

Oral bridging

In CAPELLA across cohorts 1 and 2, 79% of participants (57/72) received SUNLENCA 300 mg once every 7 days as oral bridging. A total of 13, 29, and 15 participants started oral bridging following Weeks 26, 52, and 78 injections, respectively. The median (Q1, Q3) duration of oral bridging was 19 weeks (11, 22), and 12% (7/57) received oral bridging for at least 28 weeks.

In a post-hoc analysis, rates of virologic suppression and change from baseline in CD4^+ cell counts in the subset of patients who received oral bridging were consistent before and during the oral bridging period.

16 HOW SUPPLIED/STORAGE AND HANDLING

SUNLENCA tablets, 300 mg are beige, capsule-shaped, and film-coated with "GSI" debossed on one side and "62L" on the other side. SUNLENCA tablets are available in a bottle and blister packs, packaged as follows:

Bottle

- SUNLENCA bottle contains 4 tablets (NDC 61958-3001-3). The bottle also contains a silica gel desiccant and polyester coil, and is closed with a child-resistant closure. Do not remove the desiccant packet.

Keep bottle tightly closed.

Blister Packs

- SUNLENCA 4-Tablets™ blister pack contains 4 tablets (NDC 61958-3001-1)
- SUNLENCA 5-Tablets™ blister pack contains 5 tablets (NDC 61958-3001-2)

Within the blister packs, tablets are packaged in a clear blister film sealed to a foil lidding material. The blister card is fitted between two paperboard cards, and packaged with silica gel desiccant in a sealed child-resistant flexible laminated pouch.

STORAGE AND HANDLING

Store bottle and blister packs at 20 °C – 25 °C (68 °F – 77 °F), excursions permitted to 15 °C – 30 °C (59 °F – 86 °F) (see USP Controlled Room Temperature).

Dispense and store only in original bottle or blister pack.

SUNLENCA injection is packaged in one of two different injection kits containing the following:

Vial access device injection kit (NDC 61958-3002-1):

- 2 single-dose clear glass vials, each containing sufficient volume to allow withdrawal of 463.5 mg/1.5 mL (309 mg/mL) of lenacapavir. The injection solution is sterile, preservative-free, clear, and yellow with no visible particles. Vials are sealed with a stopper and aluminium overseal with flip-off cap.
- 2 vial access devices, 2 disposable syringes, and 2 injection safety needles for subcutaneous injection (22-gauge, ½ inch).

Withdrawal needle injection kit (NDC 61958-3005-1):

- 2 single-dose clear glass vials, each containing sufficient volume to allow withdrawal of 463.5 mg/1.5 mL (309 mg/mL) of lenacapavir. The injection solution is sterile, preservative-free, clear, and yellow with no visible particles. Vials are sealed with a stopper and aluminium overseal with flip-off cap.
- 2 disposable syringes, 2 withdrawal needles (18-gauge, 1.5 inch), and 2 injection safety needles for subcutaneous injection (22-gauge, ½ inch).

The vial stoppers are not made with natural rubber latex.

STORAGE AND HANDLING

Store at 20 °C – 25 °C (68 °F – 77 °F), excursions permitted to 15 °C – 30 °C (59 °F – 86 °F).

Keep the vials in the original carton until just prior to preparation of the injections in order to protect from light.

Once the solution has been drawn into the syringes, the injections should be administered as soon as possible.

Discard any unused portion of the solution.

17 PATIENT COUNSELING INFORMATION

Advise the patient to read the FDA-approved patient labeling (Patient Information).

Drug Interactions

SUNLENCA may interact with certain drugs; therefore, advise patients to report to their healthcare provider the use of any other prescription or non-prescription medication or herbal products, including St. John's wort, during treatment with SUNLENCA [see Contraindications (4) and Drug Interactions (7)].

If SUNLENCA is discontinued, advise patients that SUNLENCA may remain in the body and affect certain other drugs for up to 9 months after receiving their last injection [see Drug Interactions (7.2, 7.3)].

Immune Reconstitution Syndrome

Advise patients to inform their healthcare provider immediately of any symptoms of infection, as in some patients with advanced HIV (AIDS), signs and symptoms of inflammation from previous infections may occur soon after anti-HIV treatment is started [see Warnings and Precautions (5.1)].

Adherence to SUNLENCA

Counsel patients about the importance of continued medication adherence and scheduled visits to maintain viral suppression and to reduce risk of loss of virologic response and development of resistance. Advise patients to contact their healthcare provider immediately if they stop taking SUNLENCA or any other drug in their antiretroviral regimen [see Dosage and Administration (2.1) and Warnings and Precautions (5.2)].

Missed Dose

Inform patients that SUNLENCA can remain in the body for up to 12 months or longer after receiving their last injection. Advise patients to contact their healthcare provider if they miss or plan to miss a scheduled injection visit and that oral SUNLENCA therapy may be used for up to 6 months to replace missed injections. Advise patients that oral dosing should be used on an interim basis only and that the maintenance injection dosage should be resumed at the earliest possible opportunity [see Dosage and Administration (2.3) and Warnings and Precautions (5.2)].

Injection Site Reactions

Inform patients that injection site reactions (ISRs), such as swelling, pain, erythema, nodule, induration, pruritus, extravasation or mass, may occur. Nodules and indurations at the injection site may take longer to resolve than other ISRs and may be persistent. Instruct patients when to contact their healthcare provider about these reactions [see Warnings and Precautions (5.3)].

Pregnancy Registry

Inform patients that there is an antiretroviral pregnancy registry to monitor fetal outcomes of pregnant individuals exposed to SUNLENCA [see Use in Specific Populations (8.1)].

Lactation

Inform individuals with HIV-1 that the potential risks of breastfeeding include: (1) HIV-1 transmission (in infants without HIV-1), (2) developing viral resistance (in infants with HIV), and (3) adverse reactions in a breastfed infant similar to those seen in adults [see Use in Specific Populations (8.2)].

SUNLENCA is a trademark of Gilead Sciences, Inc., or its related companies. All other trademarks referenced herein are the property of their respective owners.

© 2024 Gilead Sciences, Inc. All rights reserved.

PATIENT INFORMATION

SUNLENCA® (sun-LEN-kuh)
(lenacapavir)
tablets

SUNLENCA® (sun-LEN-kuh)
(lenacapavir)
injection

What is SUNLENCA?
SUNLENCA is a prescription medicine that is used with other human immunodeficiency virus-1 (HIV-1) medicines to treat HIV-1 infection in adults:

- who have received HIV-1 medicines in the past, and
- who have HIV-1 virus that is resistant to many HIV-1 medicines, and
- whose current HIV-1 medicines are failing. Your HIV-1 medicines may be failing because the HIV-1 medicines are not working or no longer work, you are not able to tolerate the side effects, or there are safety reasons why you cannot take them.

HIV-1 is the virus that causes Acquired Immune Deficiency Syndrome (AIDS).
It is not known if SUNLENCA is safe and effective in children.

Do not receive or take SUNLENCA if you also take certain other medicines called strong CYP3A inducers. Ask your healthcare provider if you are not sure.

Before receiving or taking SUNLENCA, tell your healthcare provider about all your medical conditions, including if you:

- are pregnant or plan to become pregnant. It is not known if SUNLENCA can harm your unborn baby. Tell your healthcare provider if you become pregnant during treatment with SUNLENCA.
  Pregnancy Registry: There is a pregnancy registry for women who take SUNLENCA during pregnancy. The purpose of this registry is to collect information about the health of you and your baby. Talk with your healthcare provider about how you can take part in this registry.
- are breastfeeding or plan to breastfeed. It is not known whether SUNLENCA will pass to your baby in your breast milk. Talk with your healthcare provider about the following risks to your baby from breastfeeding during treatment with SUNLENCA:
  - The HIV-1 virus may pass to your baby if your baby does not have HIV-1.
  - The HIV-1 virus may become harder to treat if your baby has HIV-1.
  - Your baby may get side effects from SUNLENCA.

Tell your healthcare provider about all the medicines you take, including prescription and over-the-counter medicines, vitamins, and herbal supplements, including St. John's wort. Some medicines may interact with SUNLENCA. Keep a list of your medicines and show it to your healthcare provider and pharmacist when you get a new medicine.

- You can ask your healthcare provider or pharmacist for a list of medicines that interact with SUNLENCA.
- Do not start a new medicine without telling your healthcare provider. Your healthcare provider can tell you if it is safe to take SUNLENCA with other medicines.
- SUNLENCA may affect certain other medicines for up to 9 months after your last injection.

How should I receive and take SUNLENCA?

- Your SUNLENCA treatment will consist of injections and tablets.
  - SUNLENCA injections will be given to you by your healthcare provider under the skin (subcutaneous injection) in your stomach-area (abdomen).
  - Take SUNLENCA tablets by mouth, with or without food.
- There are two options (Option 1 and Option 2) to start treatment with SUNLENCA. Your healthcare provider will decide which starting option is for you.
  - If Option 1 is chosen:
    - On Day 1, you will receive 2 SUNLENCA injections and take 2 SUNLENCA tablets.
    - On Day 2, you will take 2 SUNLENCA tablets.
  - If Option 2 is chosen:
    - On Day 1 and Day 2, you will take 2 SUNLENCA tablets each day.
    - On Day 8, you will take 1 SUNLENCA tablet.
    - On Day 15, you will receive 2 SUNLENCA injections.
- After completing Option 1 or Option 2, you will receive 2 SUNLENCA injections every 6 months (26 weeks) from the date of your last injection.
- Stay under the care of a healthcare provider during treatment with SUNLENCA. It is important that you attend your planned appointments to receive your injections of SUNLENCA.
- If you miss or plan to miss your scheduled every 6 months injection of SUNLENCA, call your healthcare provider right away to discuss your treatment options.
  - If you plan to miss a scheduled SUNLENCA injection, there is the option to temporarily take SUNLENCA tablets. You will take 1 SUNLENCA tablet by mouth 1 time every 7 days, until your injections resume.
  - It is important to continue SUNLENCA treatment as your healthcare provider tells you. Missing SUNLENCA treatment may cause the HIV-1 virus to change (mutate) and become harder to treat (resistant).
- Tell your healthcare provider right away if you stop treatment with SUNLENCA or stop treatment with any other HIV-1 medicines. If you stop treatment with SUNLENCA you will need other medicines to treat your HIV-1 infection. If you do not take other HIV-1 medicines, the amount of virus in your blood may increase and the virus may become harder to treat. Call your healthcare provider right away to discuss your treatment options.
- If you take too many SUNLENCA tablets, call your healthcare provider or go to the nearest hospital emergency room right away.

What are the possible side effects of SUNLENCA?
SUNLENCA may cause serious side effects, including:

- Changes in your immune system (Immune Reconstitution Syndrome) can happen when you start taking HIV-1 medicines. Your immune system may get stronger and begin to fight infections that have been hidden in your body for a long time. Tell your healthcare provider right away if you start having any new symptoms after starting your HIV-1 medicine.
- Injection site reactions may happen when you receive SUNLENCA injections and may include swelling, pain, redness, skin hardening, small mass or lump, and itching. Hardened skin or lumps at the injection site usually can be felt but not seen. If you develop hardened skin or a lump, it may take longer than other reactions at the injection site to go away, and the injection site may not completely heal on its own. Tell your healthcare provider if you have any injection site reactions.

The most common side effects of SUNLENCA are nausea and injection site reactions.
These are not all of the possible side effects of SUNLENCA.
Call your doctor for medical advice about side effects. You may report side effects to FDA at 1-800-FDA-1088.

How should I store SUNLENCA tablets?

- Store SUNLENCA tablets at room temperature between 68 °F to 77 °F (20 °C to 25 °C).
- SUNLENCA bottle contains a desiccant packet to help keep your medicine dry (protect it from moisture). Keep the desiccant packet in the bottle. Do not eat the desiccant packet.
- Keep SUNLENCA tablets in their original bottle or blister pack.
- Keep the bottle tightly closed.

Keep SUNLENCA and all medicines out of reach of children.

General information about the safe and effective use of SUNLENCA.
Medicines are sometimes prescribed for purposes other than those listed in a Patient Information leaflet. Do not use SUNLENCA for a condition for which it was not prescribed. Do not give SUNLENCA to other people, even if they have the same symptoms you have. It may harm them. You can ask your pharmacist or healthcare provider for information about SUNLENCA that is written for health professionals.

What are the ingredients in SUNLENCA?
Active ingredient: lenacapavir
Inactive ingredients:
SUNLENCA tablets: copovidone, croscarmellose sodium, magnesium stearate, mannitol, microcrystalline cellulose, and poloxamer 407. The tablets are film-coated with a coating material containing iron oxide black, iron oxide red, iron oxide yellow, polyethylene glycol, polyvinyl alcohol, talc, and titanium dioxide.
SUNLENCA injection: polyethylene glycol 300 and water for injection.
Manufactured and distributed by: Gilead Sciences, Inc. Foster City, CA 94404
SUNLENCA is a trademark of Gilead Sciences, Inc., or its related companies. All other trademarks referenced herein are the property of their respective owners.
© 2024 Gilead Sciences, Inc. All rights reserved. 215973-GS-004/IFU-001/IFU-WD-000
For more information, call 1-800-445-3235 or go to www.SUNLENCA.com.

This Patient Information has been approved by the U.S. Food and Drug Administration.

Revised: 11/2024

PRINCIPAL DISPLAY PANEL - 300 mg Tablet Blister Pack Pouch Carton

NDC 61958-3001-1

Sunlenca®
(lenacapavir) tablets
300 mg per tablet

1 pouch containing 4 tablets

Each tablet contains: 300 mg of lenacapavir
(present as 306.8 mg lenacapavir sodium).

Store at 20 °C - 25 °C (68 °F - 77 °F).

Dispense only in original container.

Recommended Dosage: See prescribing information.

KEEP OUT OF THE REACH OF CHILDREN

GILEAD

Manufactured for:
Gilead Sciences, Inc.
Foster City, CA 94404
Made in Canada

© 2022 Gilead Sciences, Inc.

PRINCIPAL DISPLAY PANEL - 5 Tablet Blister Pack Pouch Carton

NDC 61958-3001-2

Sunlenca®
(lenacapavir) tablets
300 mg per tablet

1 pouch containing 5 tablets

Each tablet contains: 300 mg of lenacapavir
(present as 306.8 mg lenacapavir sodium).

Store at 20 °C - 25 °C (68 °F - 77 °F).

Dispense only in original container.

Recommended Dosage: See prescribing information.

KEEP OUT OF THE REACH OF CHILDREN

Talk to your healthcare provider before taking
Sunlenca tablets.

Your healthcare provider will tell you when to take
Sunlenca tablets.

GILEAD

Manufactured for:
Gilead Sciences, Inc.
Foster City, CA 94404
Made in Canada

© 2022 Gilead Sciences, Inc.

PRINCIPAL DISPLAY PANEL - 4 Tablet Bottle Label

NDC 61958-3001-3
4 tablets

Sunlenca®
(lenacapavir) tablets
300 mg per tablet

Talk to your healthcare provider
before taking Sunlenca tablets.

Your healthcare provider will tell you
when to take Sunlenca tablets.

PRINCIPAL DISPLAY PANEL - Kit Carton

Rx only
NDC 61958-3002-1

Sunlenca®
(lenacapavir) injection

463.5 mg/1.5 mL (309 mg/mL)

For Subcutaneous Injection

Contents

- 2 x 1.5 mL lenacapavir single-dose vials
- 2 vial access devices
- 2 syringes
- 2 injection needles (22 gauge, 1/2 inch)
- Prescribing Information
- Instructions for Use
- Patient Information

Both 463.5 mg/1.5 mL (2 single-dose vials) must be
administered to receive the 927 mg dose.

For Healthcare Professional administration only.

GILEAD

PRINCIPAL DISPLAY PANEL - Kit Carton - 3005

Rx only
NDC 61958-3005-1

Sunlenca®
(lenacapavir) injection

463.5 mg/1.5 mL (309 mg/mL)

For Subcutaneous Injection

Contents

- 2 x 1.5 mL lenacapavir single-dose vials
- 2 withdrawal needles (18 gauge, 1½ inch)
- 2 syringes
- 2 injection needles (22 gauge, ½ inch)
- Prescribing Information
- Instructions for Use
- Patient Information

Both 463.5 mg/1.5 mL (2 single-dose vials) must be
administered to receive the 927 mg dose.

For Healthcare Professional administration only.

GILEAD